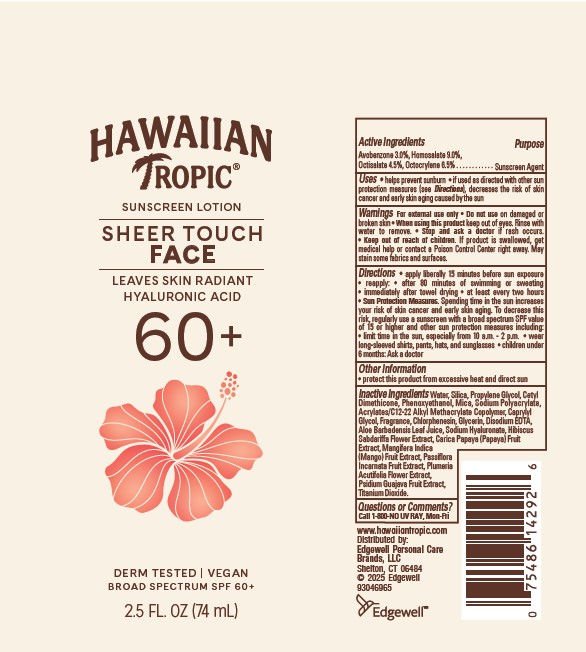 DRUG LABEL: HAWAIIAN TROPIC
NDC: 63354-611 | Form: LOTION
Manufacturer: Edgewell Personal Care Brands LLC
Category: otc | Type: HUMAN OTC DRUG LABEL
Date: 20250928

ACTIVE INGREDIENTS: OCTOCRYLENE 6.5 g/100 g; HOMOSALATE 9 g/100 g; AVOBENZONE 3 g/100 g; OCTISALATE 4.5 g/100 g
INACTIVE INGREDIENTS: SODIUM POLYACRYLATE (2500000 MW); CHLORPHENESIN; MICA; GLYCERIN; ALOE VERA LEAF; HIBISCUS SABDARIFFA FLOWER; MANGO; PASSIFLORA INCARNATA FRUIT; GUAVA; EDETATE DISODIUM; PAPAYA; PROPYLENE GLYCOL; HYALURONATE SODIUM; WATER; TITANIUM DIOXIDE; PLUMERIA RUBRA FLOWER; PHENOXYETHANOL; SILICON DIOXIDE; CAPRYLYL GLYCOL

Active Ingredients

Avobenzone 3.0%, Homosalate 9.0%, Octisalate 4.5%, Octocrylene 6.5%

Purpose

Sunscreen Agent

Uses

• helps prevent sunburn • if used as directed with other sun protection measures (see Directions), decreases the risk of skin cancer and early skin aging caused by the sun

Warnings

For external use only

May stain some fabrics and surfaces.

Do not use

on damaged or broken skin

When using

this product keep out of eyes. Rinse with water to remove.

Stop and ask a doctor

if rash occurs.

Keep out of reach of children.

If product is swallowed, get medical help or contact a Poison Control Center right away.

Directions

• apply liberally 15 minutes before sun exposure • reapply: • after 80 minutes of swimming or sweating • immediately after towel drying • at least every two hours • Sun Protection Measures. Spending time in the sun increases your risk of skin cancer and early skin aging. To decrease this risk, regularly use a sunscreen with a broad spectrum SPF value of 15 or higher and other sun protection measures including: • limit time in the sun, especially from 10 a.m. - 2 p.m. • wear long-sleeved shirts, pants, hats, and sunglasses • children under 6 months: Ask a doctor

Other Information

• protect this product from excessive heat and direct sun

Inactive Ingredients

Water, Silica, Propylene Glycol, Cetyl Dimethicone, Phenoxyethanol, Mica, Sodium Polyacrylate, Acrylates/C12-22 Alkyl Methacrylate Copolymer, Caprylyl Glycol, Fragrance, Chlorphenesin, Glycerin, Disodium EDTA, Aloe Barbadensis Leaf Juice, Sodium Hyaluronate, Hibiscus Sabdariffa Flower Extract, Carica Papaya (Papaya) Fruit Extract, Mangifera Indica (Mango) Fruit Extract, Passiflora Incarnata Fruit Extract, Plumeria Acutifolia Flower Extract, Psidium Guajava Fruit Extract, Titanium Dioxide.

Questions or Comments?

Call 1-800-NO UV RAY, Mon-Fri

Principle Display Panel

HAWAIIAN
TROPIC
SUNSCREEN LOTION
SHEER TOUCH
FACE
LEAVES SKIN RADIANT
HYALURONIC ACID
60+
DERM TESTED | VEGAN
BROAD SPECTRUM SPF 60+
2.5 FL. OZ (74 mL)